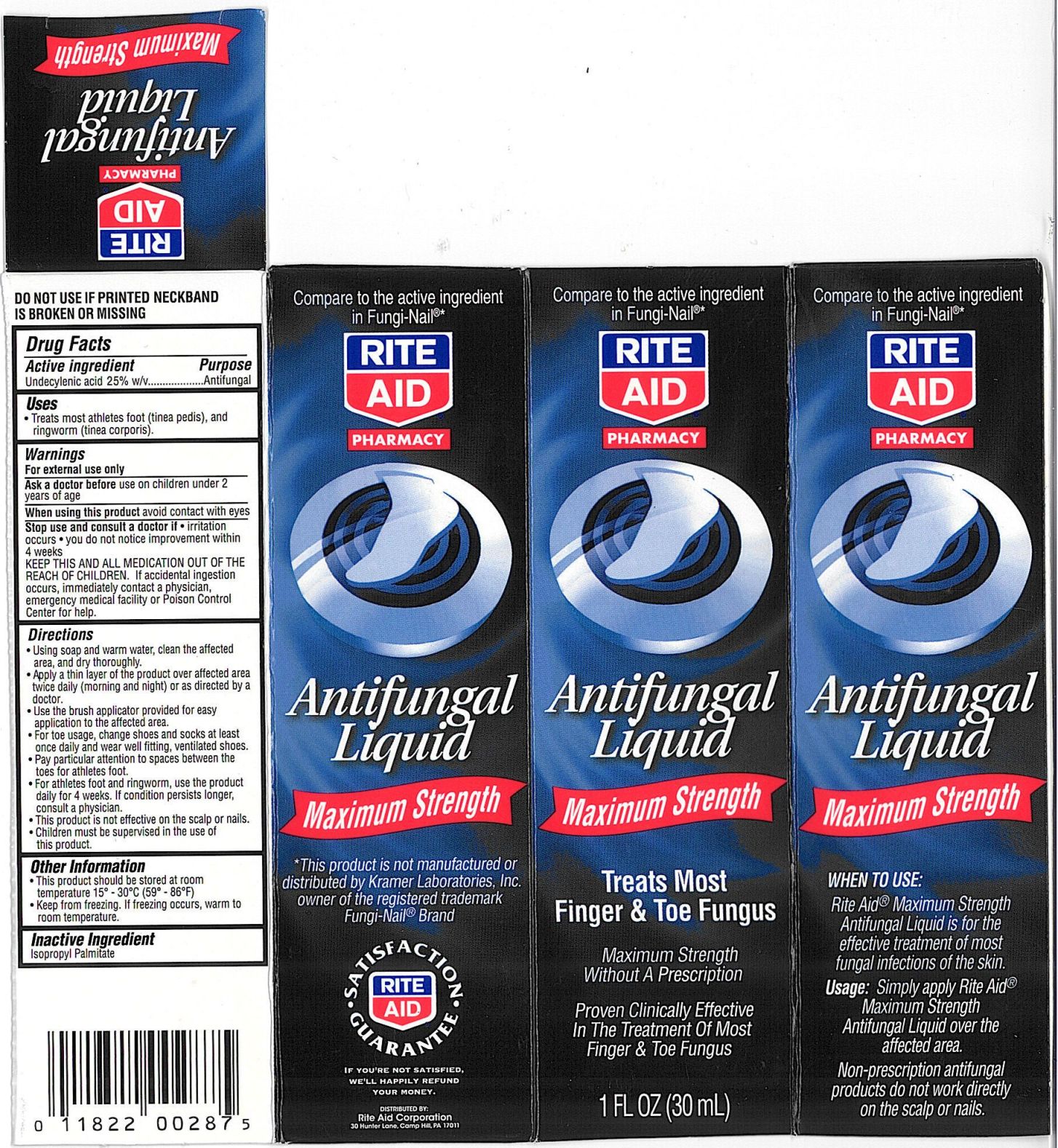 DRUG LABEL: Rite Aid Fungal 
NDC: 11822-0250 | Form: LIQUID
Manufacturer: Rite Aid Corporation
Category: otc | Type: HUMAN OTC DRUG LABEL
Date: 20110216

ACTIVE INGREDIENTS: UNDECYLENIC ACID 288 mg/1 mL
INACTIVE INGREDIENTS: ISOPROPYL PALMITATE 712 mg/1 mL

drug facts

ACTIVE INGREDIENT

Section from Carton Label Follows:
Active ingredient Purpose
Undecylenic acid 25% w/v.......Antifungal

PURPOSE

Section from Carton Label Follows:
Active ingredient Purpose
Undecylenic Acid 25% w/v.................Antifungal
Uses
Treats most athletes foot (tinea pedis)
and ringworm (tinea corporis)

KEEP OUT OF REACH OF CHILDREN

Section from Warnings section of Carton label follows:
KEEP THIS AND ALL MEDICATION OUT
OF THE REACH OF CHILDREN
If accidental ingestion occurs,
immediately contact a physician,
emergency medical facility or Poison
Control Center for help.

INDICATIONS AND USAGE

Section from Directions portion of carton label follows:
Directions
- Using soap and water, clean the
affected area and dry thoroughly
- apply a thin layer of the product over
affected area twice daily (morning and
night) or as directed by a doctor.
- Use the brush applicator provided for
easy application to the affected area
- For toe usage, change shoes and socks
at least once daily and wear well fitting,
ventilated shoes
- Pay particular attention to spaces
between the toes for athletes foot
- For athletes foot and ringworm, use the
product daily for 4 weeks. If condition
persists longer, consult a physician
- This product is not effective on the scalp
or nails
- Children must be supervised in the use
of this product

From Warnings Section of Carton Label:
Warnings For external use only.
______________________________
Ask a doctor before use on children
under 2 years of age
____________________________________
When using this productavoid contact
with the eyes
____________________________________
Stop use and consult a doctor if
- Irritation occurs - you do not notice
improvement within 4 weeks
____________________________________
KEEP THIS AND ALL MEDICATION OUT
OF THE REACH OF CHILDREN
If accidental ingestion occurs,
immediately contact a physician,
emergency medical facility or Poison
Control Center for help.

DOSAGE AND ADMINISTRATION

Section from Directions portion of carton label follows:
Directions
- Using soap and water, clean the
affected area and dry thoroughly
- apply a thin layer of the product over
affected area twice daily (morning and
night) or as directed by a doctor.
- Use the brush applicator provided for
easy application to the affected area
- For toe usage, change shoes and socks
at least once daily and wear well fitting,
ventilated shoes
- Pay particular attention to spaces
between the toes for athletes foot
- For athletes foot and ringworm, use the
product daily for 4 weeks. If condition
persists longer, consult a physician
- This product is not effective on the scalp
or nails
- Children must be supervised in the use
of this product

From Inactive Ingredients section of Carton Label:
Inactive Ingredients Isopropyl Palmitate